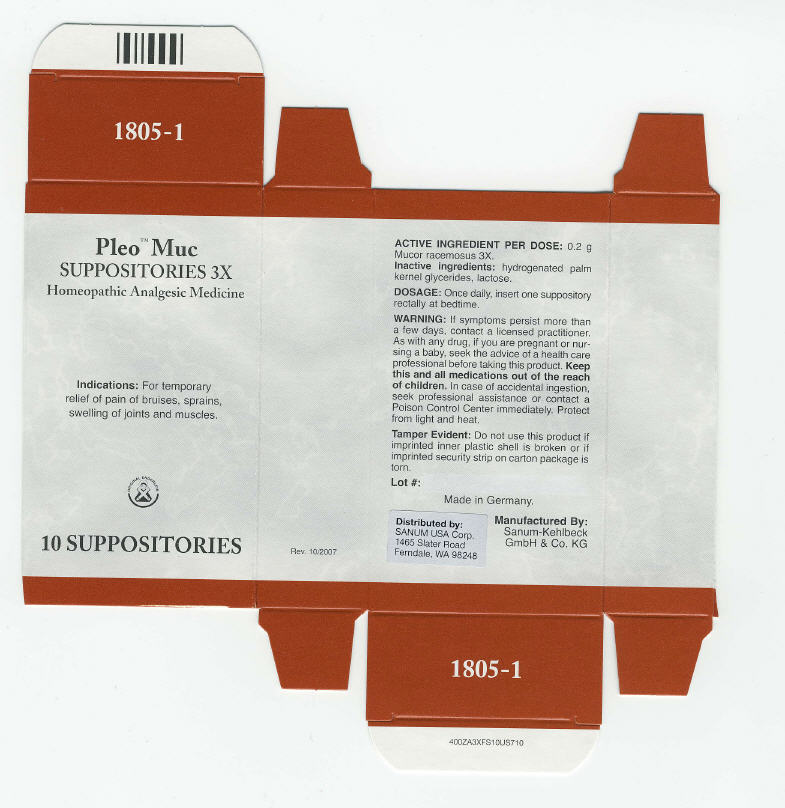 DRUG LABEL: Pleo Muc
NDC: 60681-1805 | Form: SUPPOSITORY
Manufacturer: Sanum Kehlbeck GmbH & Co. KG
Category: homeopathic | Type: HUMAN OTC DRUG LABEL
Date: 20091111

ACTIVE INGREDIENTS: mucor racemosus 3 [hp_X]/1 1
INACTIVE INGREDIENTS: lactose

Pleo™ Muc
SUPPOSITORIES 3X

Homeopathic Analgesic Medicine

10 SUPPOSITORIES

Indications

For temporary relief of pain of bruises, sprains, swelling of joints and muscles.

ACTIVE INGREDIENT PER DOSE

0.2 g Mucor racemosus 3X.

Inactive ingredients

hydrogenated palm kernel glycerides, lactose.

DOSAGE

Once daily, insert one suppository rectally at bedtime.

WARNING

If symptoms persist more than a few days, contact a licensed practitioner. As with any drug, if you are pregnant or nursing a baby, seek the advice of a health care professional before taking this product.

KEEP OUT OF REACH OF CHILDREN

Keep this and all medications out of the reach of children. In case of accidental ingestion, seek professional assistance or contact a Poison Control Center immediately.

STORAGE AND HANDLING

Protect from light and heat.

Tamper Evident

Do not use this product if imprinted inner plastic shell is broken or if imprinted security strip on carton package is torn.

Made in Germany.

Distributed by:
SANUM USA Corp.
1465 Slater Road
Ferndale, WA 98248

Manufactured By:
Sanum-Kehlbeck
GmbH & Co. KG

Rev. 10/2007

PRINCIPAL DISPLAY PANEL - 10 Suppository Carton

Pleo™ Muc
SUPPOSITORIES 3X

Homeopathic Analgesic Medicine

Indications: For temporary
relief of pain of bruises, sprains,
swelling of joints and muscles.

ORIGINAL ENDERLEIN

10 SUPPOSITORIES